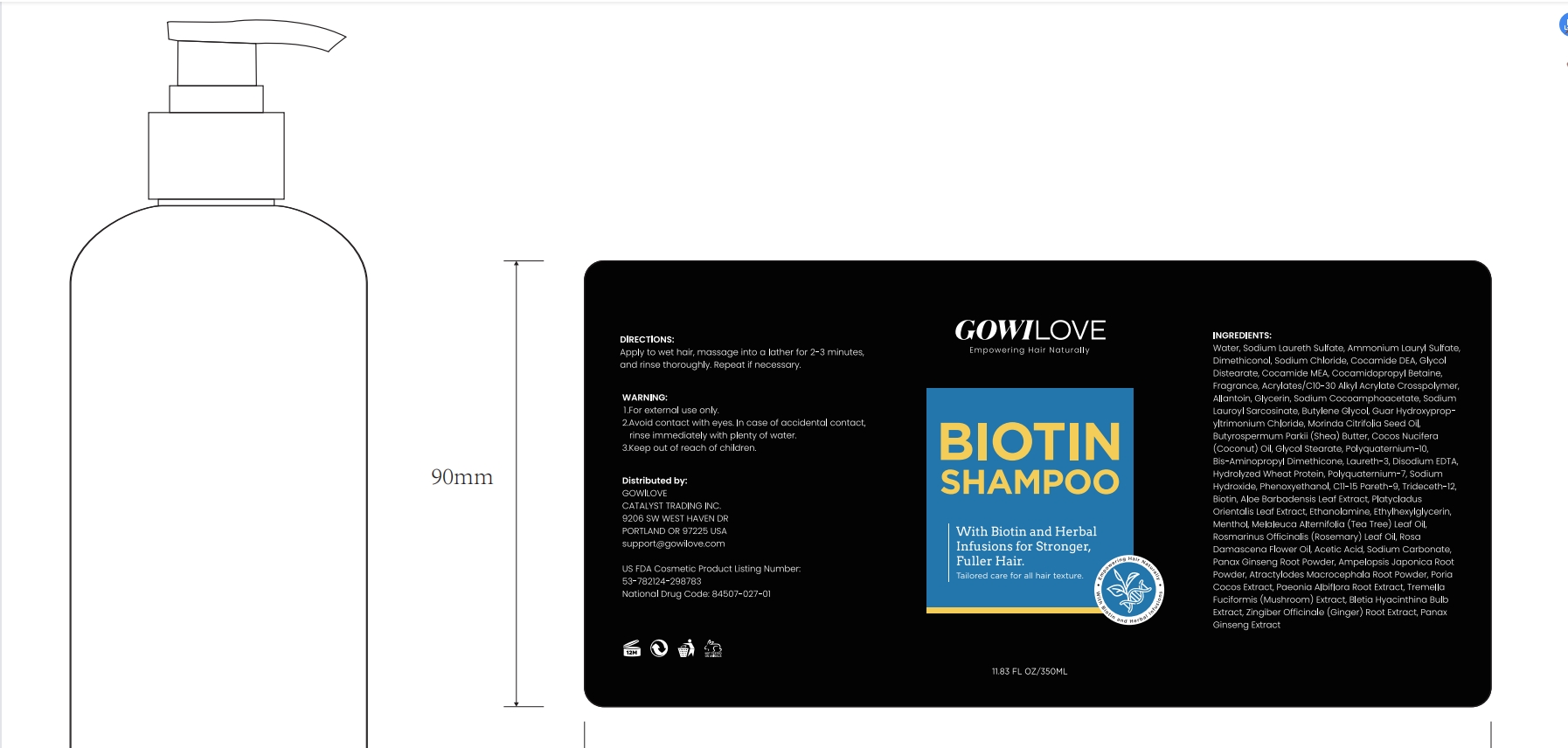 DRUG LABEL: GOWILOVE Biotion Shampoo.
NDC: 84507-031 | Form: SHAMPOO
Manufacturer: Guangdong Miaolian Cosmetics Co., Ltd.
Category: otc | Type: HUMAN OTC DRUG LABEL
Date: 20250220

ACTIVE INGREDIENTS: ROSMARINUS OFFICINALIS (ROSEMARY) LEAF OIL 0.001 mg/100 mL; MELALEUCA ALTERNIFOLIA (TEA TREE) LEAF OIL 0.001 mg/100 mL; ROSA DAMASCENA FLOWER OIL 0.001 mg/100 mL
INACTIVE INGREDIENTS: COCAMIDOPROPYL BETAINE; LAURETH-3; BUTYLENE GLYCOL; COCOS NUCIFERA (COCONUT) OIL; PAEONIA ALBIFLORA FLOWER; WOLFIPORIA COCOS WHOLE; TRIDECETH-12; CETRIMONIUM CHLORIDE; GUAR HYDROXYPROPYLTRIMONIUM CHLORIDE; BUTYROSPERMUM PARKII (SHEA) BUTTER; MENTHOL; ATRACTYLODES MACROCEPHALA ROOT; SODIUM LAURETH SULFATE; PHENOXYETHANOL; PLATYCLADUS ORIENTALIS LEAF; ALOE BARBADENSIS LEAF; SODIUM COCOAMPHOACETATE; COCAMIDE MEA; POLYQUATERNIUM-10 (125 MPA.S AT 2%); EDETATE DISODIUM; SODIUM CHLORIDE; ACRYLATES/C10-30 ALKYL ACRYLATE CROSSPOLYMER (60000 MPA.S); TREMELLA FUCIFORMIS WHOLE; PANAX GINSENG WHOLE; AMMONIUM LAURYL SULFATE; DIMETHICONOL (40 CST); ETHYLHEXYLGLYCERIN; HYDROLYZED WHEAT PROTEIN (ENZYMATIC, 3000 MW); CAPRYLYL GLYCOL; ZINGIBER OFFICINALE (GINGER) ROOT OIL; MORINDA CITRIFOLIA SEED OIL; GLYCOL DISTEARATE; SODIUM LAUROYL SARCOSINATE; GLYCOL STEARATE; POLYQUATERNIUM-7; ETHANOLAMINE; FRAGRANCE 13576; ALLANTOIN; SODIUM HYDROXIDE; SODIUM CARBONATE; BIOTIN; PANAX GINSENG ROOT; AMPELOPSIS JAPONICA ROOT; WATER; GLYCERIN; AMODIMETHICONE (240 CST); COCAMIDE DEA; DECYLENE GLYCOL

DOSAGE AND ADMINISTRATION

Moisturize the hair with warm water. Apply shampoo containing onion, rosemary, and biotin.Massage the scalp gently and continue to rub all over the hair with plenty of water until thoroughly rinsed.

WARNINGS

Keep in a cool, dry place, and protect from moisture and sunlight.

INACTIVE INGREDIENT

WATER
SODIUM LAURETH SULFATE
AMMONIUM LAURYL SULFATE
DIMETHICONOL
PHENOXYETHANOL
ETHYLHEXYLGLYCERIN
COCAMIDOPROPYL BETAINE
SODIUM CHLORIDE
LAURETH-3
COCAMIDE DEA
GLYCERIN
MORINDA CITRIFOLIA SEED OIL
GLYCOL DISTEARATE
GLYCOL STEARATE
BUTYLENE GLYCOL
HYDROLYZED WHEAT PROTEIN
POLYQUATERNIUM-7
SODIUM COCOAMPHOACETATE
COCAMIDE MEA
ETHANOLAMINE
SODIUM LAUROYL SARCOSINATE
AMODIMETHICONE
TRIDECETH-12
CETRIMONIUM CHLORIDE
DECYLENE GLYCOL
CAPRYLYL GLYCOL
FRAGRANCE
ACRYLATES/C10-30 ALKYL ACRYLATE CROSSPOLYMER
ALLANTOIN
GUAR HYDROXYPROPYLTRIMONIUM CHLORIDE
ALOE BARBADENSIS LEAF EXTRACT
BUTYROSPERMUM PARKII (SHEA) BUTTER
COCOS NUCIFERA (COCONUT) OIL
PLATYCLADUS ORIENTALIS LEAF EXTRACT
POLYQUATERNIUM-10
DISODIUM EDTA
SODIUM HYDROXIDE
SODIUM CARBONATE
BIOTIN
PANAX GINSENG ROOT POWDER
ATRACTYLODES MACROCEPHALA ROOT POWDER
TREMELLA FUCIFORMIS (MUSHROOM) EXTRACT
BLETIA HYACINTHINA BULB EXTRACT
PAEONIA ALBIFLORA ROOT EXTRACT
PORIA COCOS EXTRACT
AMPELOPSIS JAPONICA ROOT POWDER
PANAX GINSENG EXTRACT
ZINGIBER OFFICINALE (GINGER) ROOT EXTRACT
MENTHOL

INDICATIONS AND USAGE

Improves the scalp environment, repairs damaged hair, and moisturizes hair. This product contains plant essences to repair the scalp barrier, provide a non-greasy moisturizing effect, and make hair look full and natural.

KEEP OUT OF REACH OF CHILDREN

Keep out of the reach of children. Avoid contact with the eyes. If you observe an unfavorable reaction, suspend use and, if it persists, consult a doctor. Keep the bottle closed and store in a cool place.

PURPOSE

Improves the scalp environment, repairs damaged hair, and moisturizes hair.

ACTIVE INGREDIENT

ROSMARINUS OFFICINALIS (ROSEMARY) LEAF OIL -------0.001
MELALEUCA ALTERNIFOLIA (TEA TREE) LEAF OIL -------0.001
ROSA DAMASCENA FLOWER OIL -------0.001